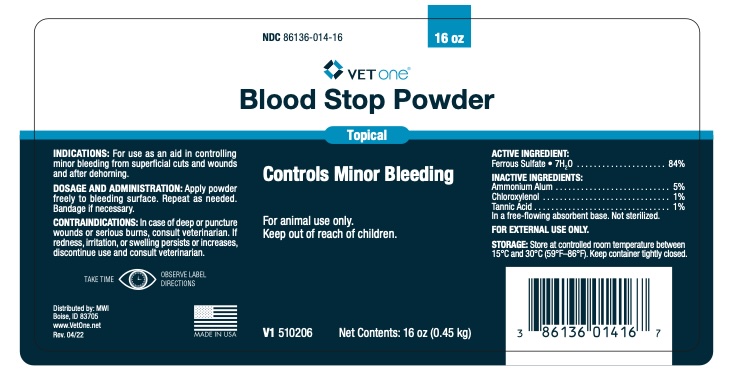 DRUG LABEL: Blood Stop Powder
NDC: 86136-014 | Form: POWDER
Manufacturer: MWI (VetOne)
Category: animal | Type: OTC ANIMAL DRUG LABEL
Date: 20241025

ACTIVE INGREDIENTS: FERROUS SULFATE 381.36 g/454 g

DOSAGE AND ADMINISTRATION

Apply powder freely to bleeding surface. Repeat as needed. Bandage if necessary.

CONTRAINDICATIONS

In case of deep or puncture wounds or serious burns, consult veterinarian. If redness, irritation, or swelling persists or increases, discontinue use and consult veterinarian.

CONTENTS

Ferrous Sulfate • 7H2O 84.0%, Ammonium Alum 5%, Chloroxylenol 1%, Tannic Acid 1%, In a free-flowing absorbent base. Not sterilized.

For external use only.

STORAGE AND HANDLING

Store at controlled room temperature between 15o-30oC (59o-86oF)

Keep container tightly closed.

TAKE TIME TO OBSERVE LABEL DIRECTIONS